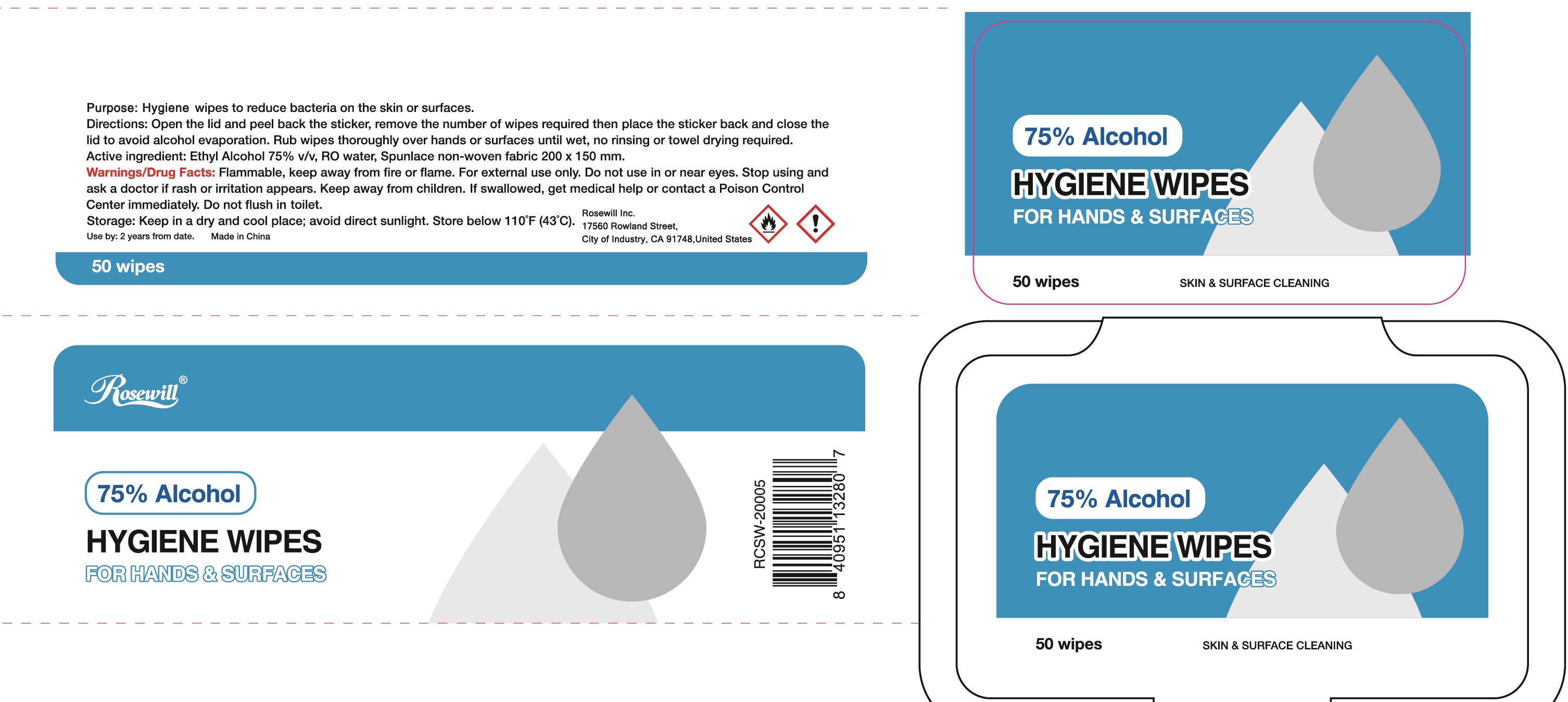 DRUG LABEL: Rosewill Hygiene Wipes
NDC: 78724-002 | Form: SWAB
Manufacturer: Jiebao Daily Chemical (Xiangxi)Co.,Ltd
Category: otc | Type: HUMAN OTC DRUG LABEL
Date: 20200604

ACTIVE INGREDIENTS: ALCOHOL 75 g/100 g
INACTIVE INGREDIENTS: WATER

Hygiene Wipes

Active Ingredient

Ethyl Alcohol 75%

Purpose

Antimicrobial

USE

To reduce bacteria on the skin or surface.

Warning

- Flammable, keep away from fire or flame. For external use only.
- When using this product, Do not use in or near the eyes. In case of contact, rinse eyes thoroughly with water.

- Stop use and ask a doctor, if rash and irritaion appears.
- Do not flush in toilet.

Other Information：

Keep in a dry and cool place; avoid direct sunlight. Store below 110℉ (43 ℃).

KEEP OUT OF REACH OF CHILDREN

If swallowed, get medical help or contact a Poison Contrl Center right away.

Directions

Rub wipes thoroughly over hands or surfaces until wet, no rinsing or towel drying required.

Inactive ingredients

RO Water